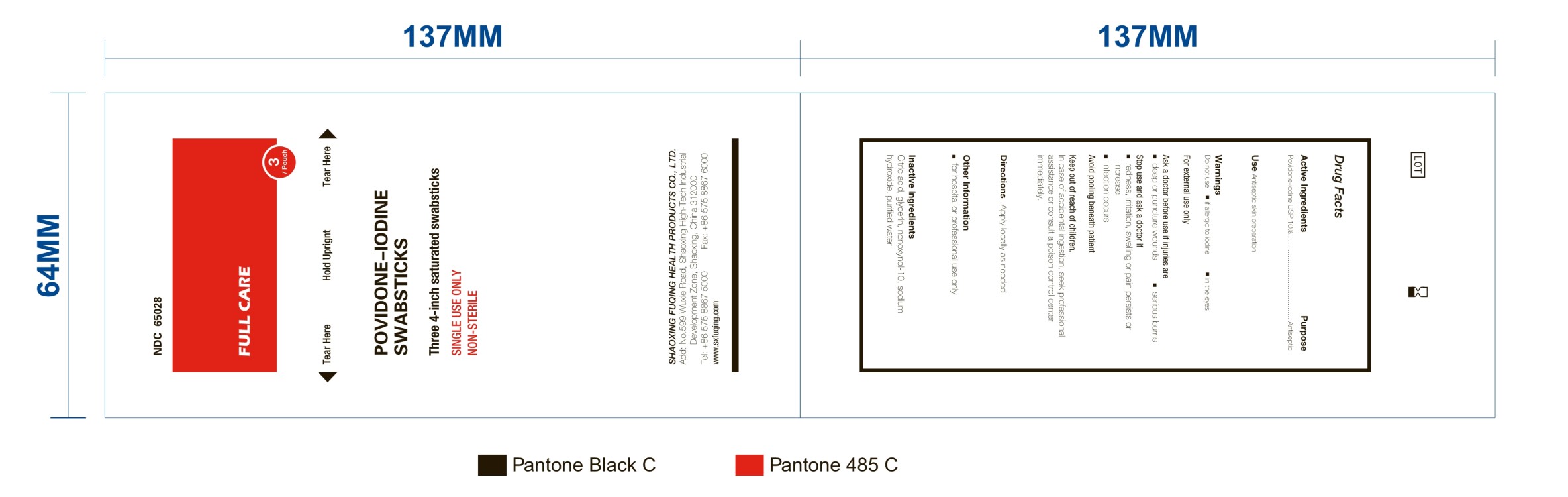 DRUG LABEL: Povidone Iodine Swabsticks
NDC: 65028-008 | Form: SWAB
Manufacturer: Shaoxing Fuqing Health Products Co., Ltd.
Category: otc | Type: HUMAN OTC DRUG LABEL
Date: 20180330

ACTIVE INGREDIENTS: POVIDONE-IODINE 0.2 g/1 1
INACTIVE INGREDIENTS: WATER; CITRIC ACID MONOHYDRATE; SODIUM HYDROXIDE; GLYCERIN; NONOXYNOL-10

Active Ingredient: Povidone-Iodine USP (10%)

Purpose: Antiseptic

INDICATIONS AND USAGE

Use: Antiseptic skin preparation

Warnings:

Do not use

- if allergic to iodine
- in the eyes

For external use only

Avoid "pooling" beneath patients.

Keep out of reach of children. In case of accidental ingestion, seek professional assistance or consult a poison control center immediately

Ask a doctor before use if injuries are

- deep or puncture wounds
- serious burns

Stop use and ask a doctor if

- redness, irritation, swelling, or pain persists or increases
- infection occurs

DOSAGE AND ADMINISTRATION

Apply locally as need

Other information

- For hospital or professional use only

Inactive Ingredient

Citric Acid, Glycerin, Nonoxyol-10, Sodium Hydroxide, Water